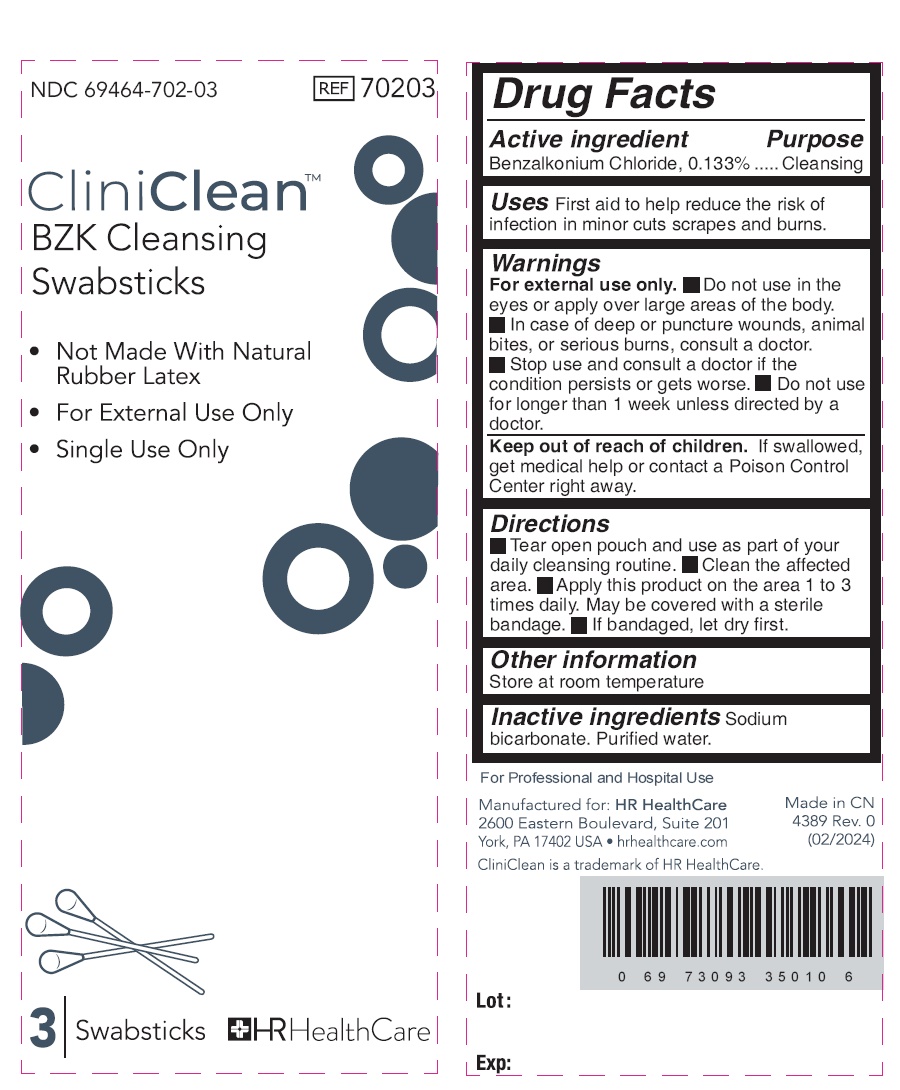 DRUG LABEL: CliniClean BZK Cleansing Swabsticks
NDC: 69464-702 | Form: LIQUID
Manufacturer: HR HealthCare
Category: otc | Type: HUMAN OTC DRUG LABEL
Date: 20240430

ACTIVE INGREDIENTS: BENZALKONIUM CHLORIDE 1.33 mg/1 g
INACTIVE INGREDIENTS: SODIUM BICARBONATE; WATER

CliniClean BZK Cleansing Swabsticks

Active ingredient

Benzalkonium Chloride, 0.133%

Purpose

Cleansing

Uses

First aid to help reduce the risk of infection in minor cuts scrapes and burns.

Warnings

For external use only.

• Do not use

in the eyes or apply over large areas of the body.

• In case of deep or puncture wounds, animal bites, or serious burns, consult a doctor.

• Stop use and consult a doctor

if the condition persists or gets worse.

• Do not use for longer than 1 week unless directed by a doctor.

Keep out of reach of children.

If swallowed, get medical help or contact a Poison Control Center right away.

Directions

- Tear open pouch and use as part of your daily cleansing routine.
- Clean the affected area.
- Apply this product on the area 1 to 3 times daily. May be covered with a sterile bandage.
- If bandaged, let dry first.

Other information

Store at room temperature

Inactive ingredients

Sodium bicarbonate. Purified water.